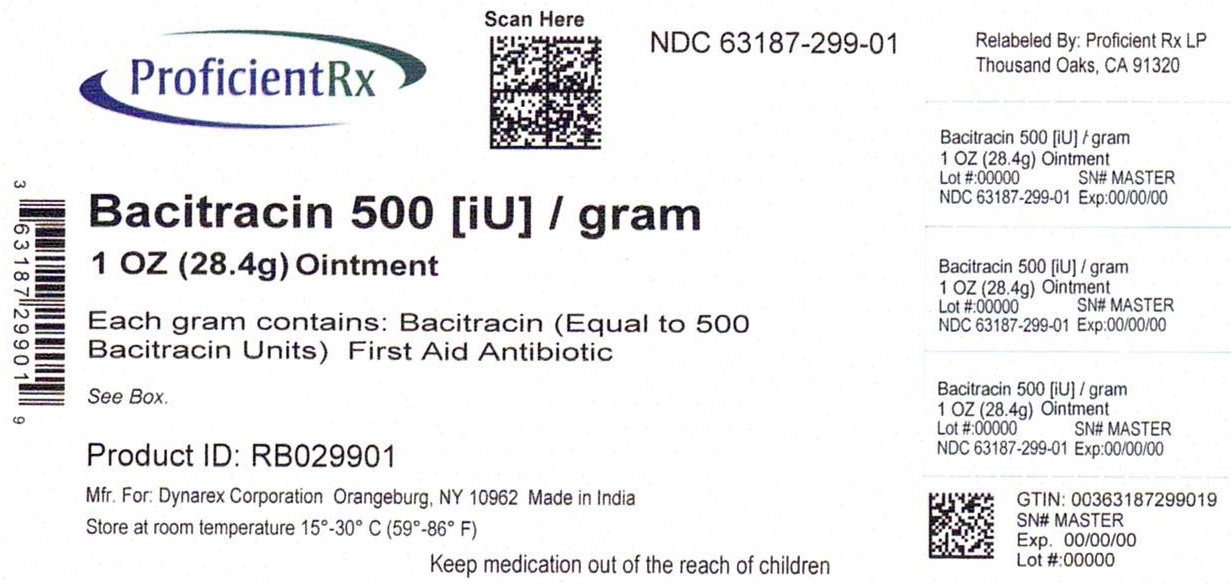 DRUG LABEL: Bacitracin
NDC: 63187-299 | Form: OINTMENT
Manufacturer: Proficient Rx LP
Category: otc | Type: HUMAN OTC DRUG LABEL
Date: 20240101

ACTIVE INGREDIENTS: BACITRACIN 500 [iU]/1 g
INACTIVE INGREDIENTS: MINERAL OIL; PETROLATUM

1162_1163_Bacitracin_Ointment

Active ingredient Purpose
Bacitracin 500 Units Antibiotic

Warnings:

For external use only

Dosage and Administration:

- clean the affected areas
- apply a small amount of product (an amount equal to the surface area of the tip of the finger) on the area 1 to 3 times daily
- may be covered with a sterile bandage

Stop use and ask a doctor if

- the condition persists or gets worse, or if a rash or other allergic reaction develops.

Do not use:

- if you are allergic to any of the ingredients
- in the eyes
- over large areas of the body
- longer than 1 week unless directed by a doctor

Keep out of reach of children

if swallowed, get medical help or contact a Poison Control Center right away

Purpose

First aid to help prevent infection in:
Minor cuts
scrapes
burns

Indications and Usage

Ask a doctor before use:

- in case of deep or puncture wounds
- animal bites
- serious burns

Other information

- store at controlled room temperature 15°-30° C (59°-86° F)

Inactive ingredients

Light Mineral Oil, White Petrolatum

Principal Display Panel

Relabeled By:

Proficient Rx LP

Thousand Oaks, CA 91320

Bacitracin Ointment:

bacitracin-galentic-ointment-01.jpg